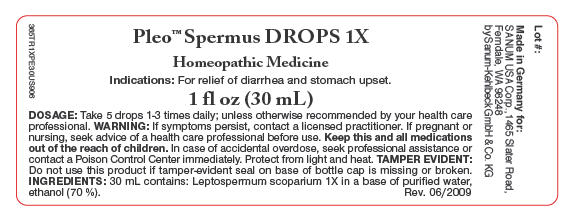 DRUG LABEL: Pleo Spermus
NDC: 60681-1311 | Form: SOLUTION/ DROPS
Manufacturer: Sanum Kehlbeck GmbH & Co. KG
Category: homeopathic | Type: HUMAN OTC DRUG LABEL
Date: 20091221

ACTIVE INGREDIENTS: Manuka Oil 1 [hp_X]/30 mL
INACTIVE INGREDIENTS: alcohol; water

Pleo™ Spermus
DROPS 1X

Homeopathic Medicine

1 fl oz
(30 mL)

Indications

For relief of diarrhea and stomach upset.

INGREDIENTS

30 mL contains: Leptospermum scoparium 1X in a base of purified water, ethanol (70%).

Tamper Evident

Use this product only if tamper-evident strip on base of bottle cap is intact.

DOSAGE

Take 5 drops, 1–3 times daily, unless otherwise recommended by your health care professional.

WARNING

If symptoms persist more than a few days, contact a licensed practitioner. As with any drug, if you are pregnant or nursing a baby, seek the advice of a health care professional before using this product.

KEEP OUT OF REACH OF CHILDREN

Keep this and all medications out of the reach of children. In case of accidental overdose, seek professional assistance or contact a Poison Control Center immediately.

STORAGE AND HANDLING

Protect from light and heat.

Made in Germany.

Distributed by:
SANUM USA Corp.
1465 Slater Road
Ferndale, WA 98248

Manufactured By:
Sanum-Kehlbeck,
GmbH & Co. KG

Rev. 08/2000

PRINCIPAL DISPLAY PANEL - 30 mL Label

Pleo™ Spermus DROPS 1X

Homeopathic Medicine

Indications: For relief of diarrhea and stomach upset.

1 fl oz (30 mL)

DOSAGE: Take 5 drops 1-3 times daily; unless otherwise recommended by your health care
professional. WARNING: If symptoms persist, contact a licensed practitioner. If pregnant or
nursing, seek advice of a health care professional before use. Keep this and all medications
out of the reach of children. In case of accidental overdose, seek professional assistance or
contact a Poison Control Center immediately. Protect from light and heat. TAMPER EVIDENT:
Do not use this product if tamper-evident seal on base of bottle cap is missing or broken.
INGREDIENTS: 30 mL contains: Leptospermum scoparium 1X in a base of purified water,
ethanol (70 %).
Rev. 06/2009